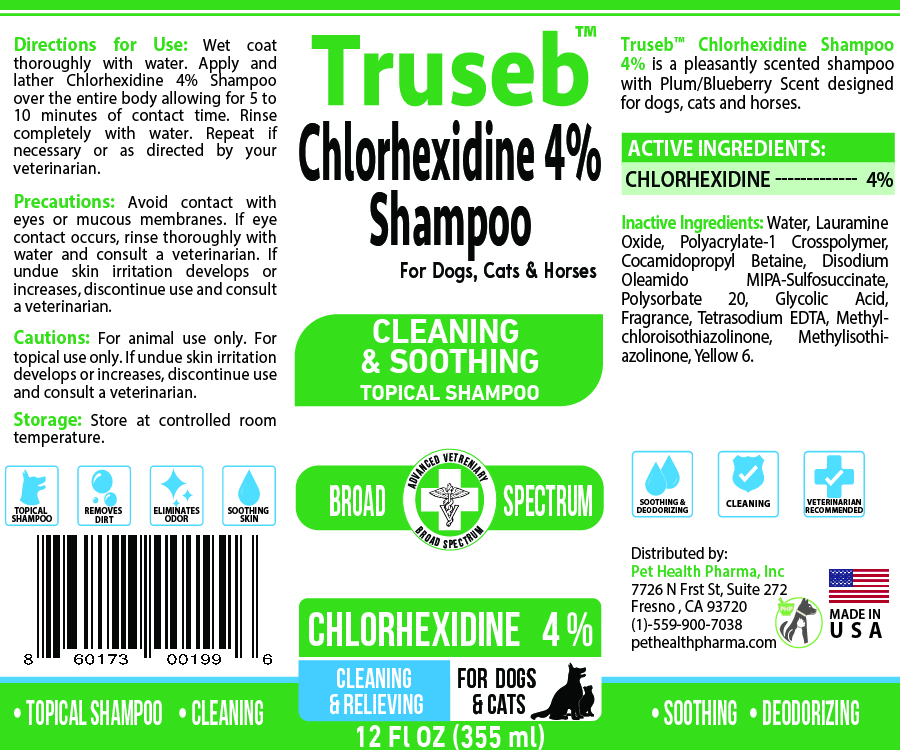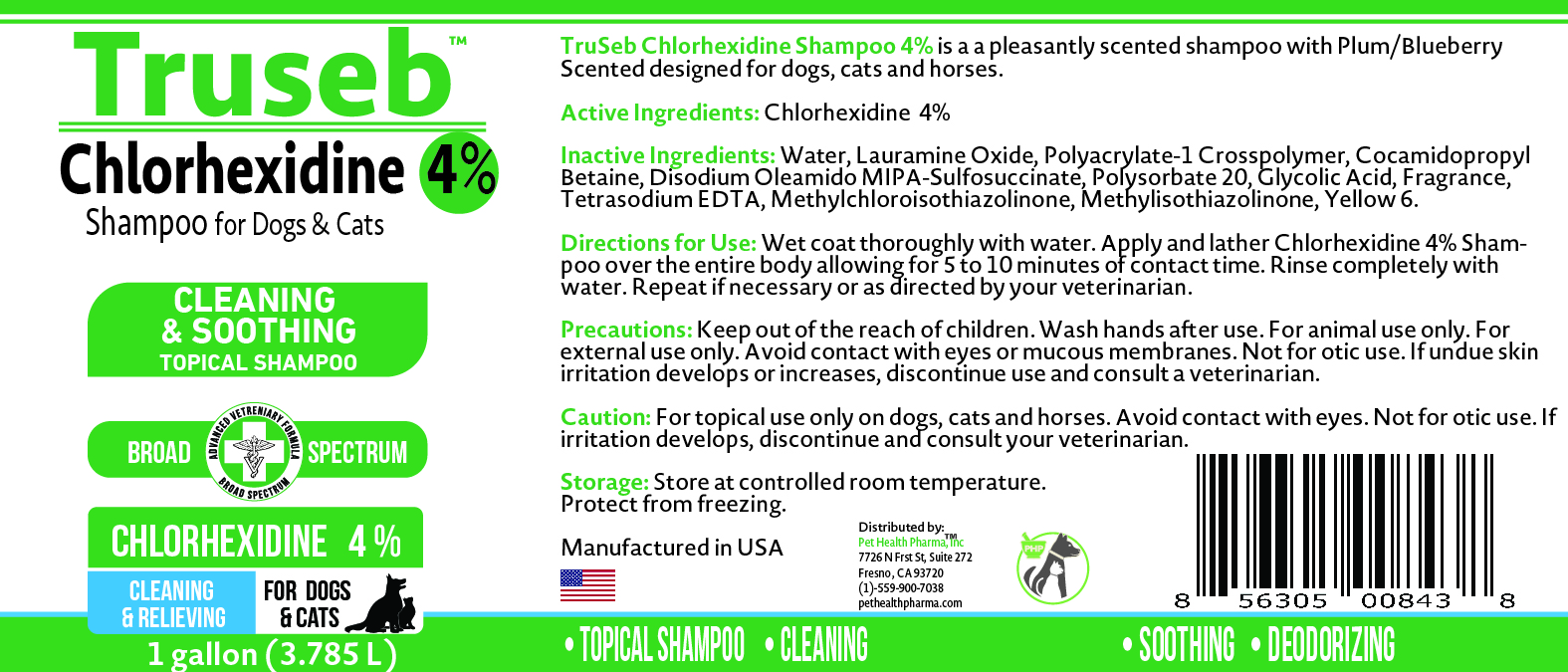 DRUG LABEL: Truseb Chlorhexidine 4% Medicated for Dogs, Cats And Horses
NDC: 86176-101 | Form: SHAMPOO
Manufacturer: Pet Health Pharma, LLC
Category: animal | Type: OTC ANIMAL DRUG LABEL
Date: 20250214

ACTIVE INGREDIENTS: CHLORHEXIDINE GLUCONATE 4 g/100 mL
INACTIVE INGREDIENTS: WATER; LAURAMINE OXIDE; POLYACRYLATE-1 CROSSPOLYMER; COCAMIDOPROPYL BETAINE; DISODIUM OLEAMIDO MIPA-SULFOSUCCINATE; POLYSORBATE 20; GLYCOLIC ACID; TETRASODIUM EDTA; METHYLCHLOROISOTHIAZOLINONE; METHYLISOTHIAZOLINONE

TRUSEB CHLORHEXIDINE 4% SHAMPOO FOR DOGS, CATS AND HORSES

Active Ingredients:

Chlorhexidine Gluconate 4%

INACTIVE INGREDIENT:

Water, Lauramine Oxide, Polyacrylate-1 Crosspolymer, Cocamidopropyl Betaine, Disodium Oleamido MIPA-Sulfosuccinate, Polysorbate 20, Glycolic Acid, Fragrance, Tetrasodium EDTA, Methylchloroisothiazolinone, Methylisothiazolinone, Yellow 6.

INDICATIONS & USAGE:

Truseb™ Chlorhexidine Shampoo 4% is a pleasantly scented shampoo with Plum/Blueberry Scent designed for dogs, cats and horses

DOSAGE & ADMINISTRATION:

Directions for Use Wet coat thoroughly with water. Apply and lather Chlorhexidine 4% Shampoo over the entire body allowing for 5 to 10 minutes of contact time. Rinse completely with water. Repeat if necessary or as directed by your veterinarian.

PRECAUTIONS:

Avoid contact with eyes or mucous membranes. If eye contact occurs, rinse thoroughly with water and consult a veterinarian. If undue skin irritation develops or increases, discontinue use and consult a veterinarian

CAUTION:

For animal use only. For topical use only. If undue skin irritation develops or increases, discontinue use and consult a veterinarian.

STORAGE:

Store at controlled room temperature. Protect from freezing.

SPL UNCLASSIFIED SECTION:

CLEANING & SOOTHING TOPICAL SHAMPOO
ADVANCED VETERINARY FORMULA
Broad Spectrum
CLEANSING & RELIEVING
• TOPICAL SHAMPOO • CLEANING • SOOTHING • DEODORIZING
for Dogs, Cats & Horses
TOPICAL SHAMPOO
REMOVES DIRT
ELIMINATES ORDER
SOOTHING SKIN
CLEANING
SOOTHING & DEODORIZING
VETERINARIAN RECOMMENDED

MADE IN USA

Distributed by:

Pet Health Pharma, Inc
7726 N Frst St, Suite 272
Fresno , CA 93720
(1)-559-900-7038
pethealthpharma.com

PACKAGE LABEL

Packaging

Add image transcription here...

Add image transcription here...